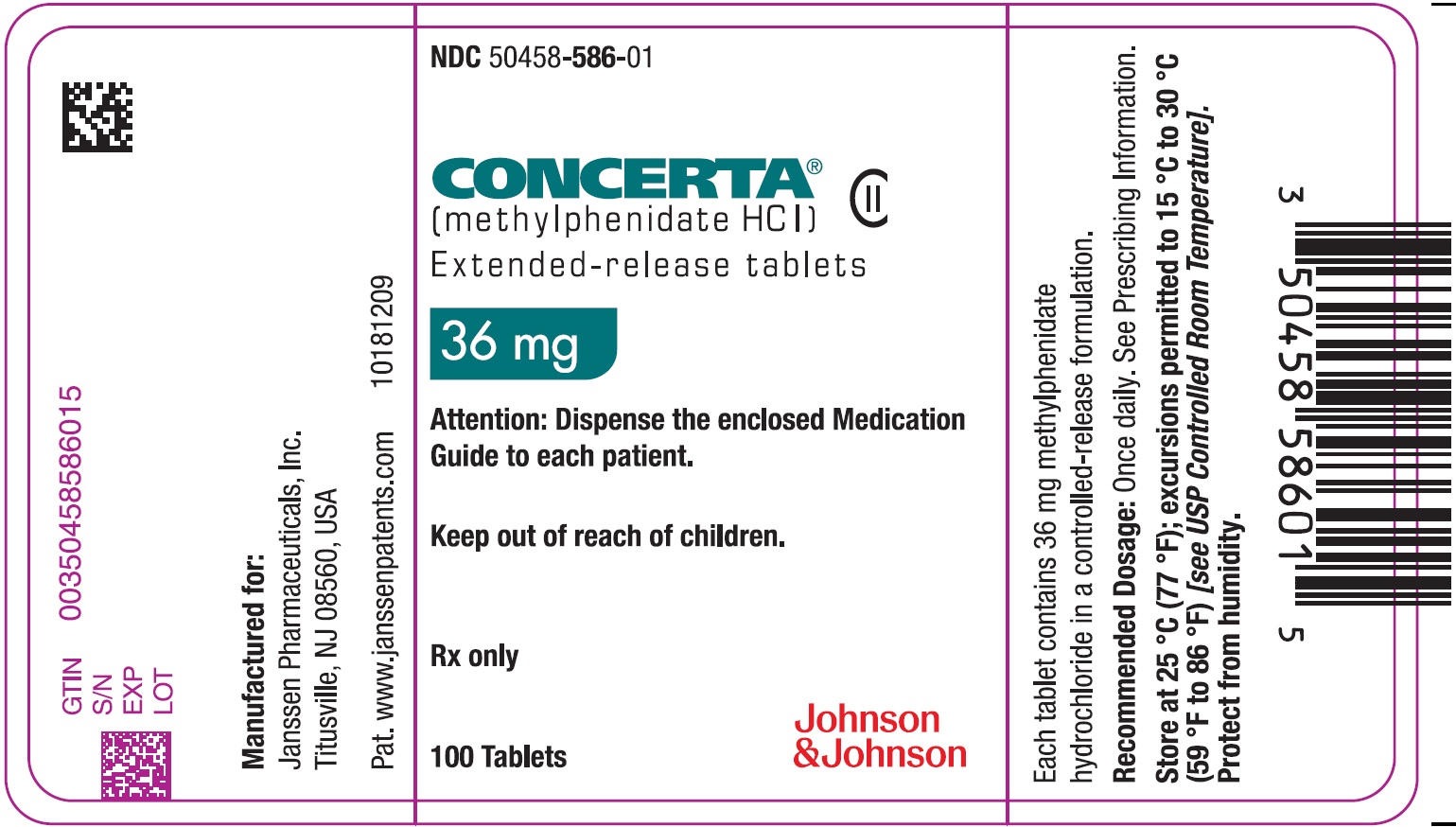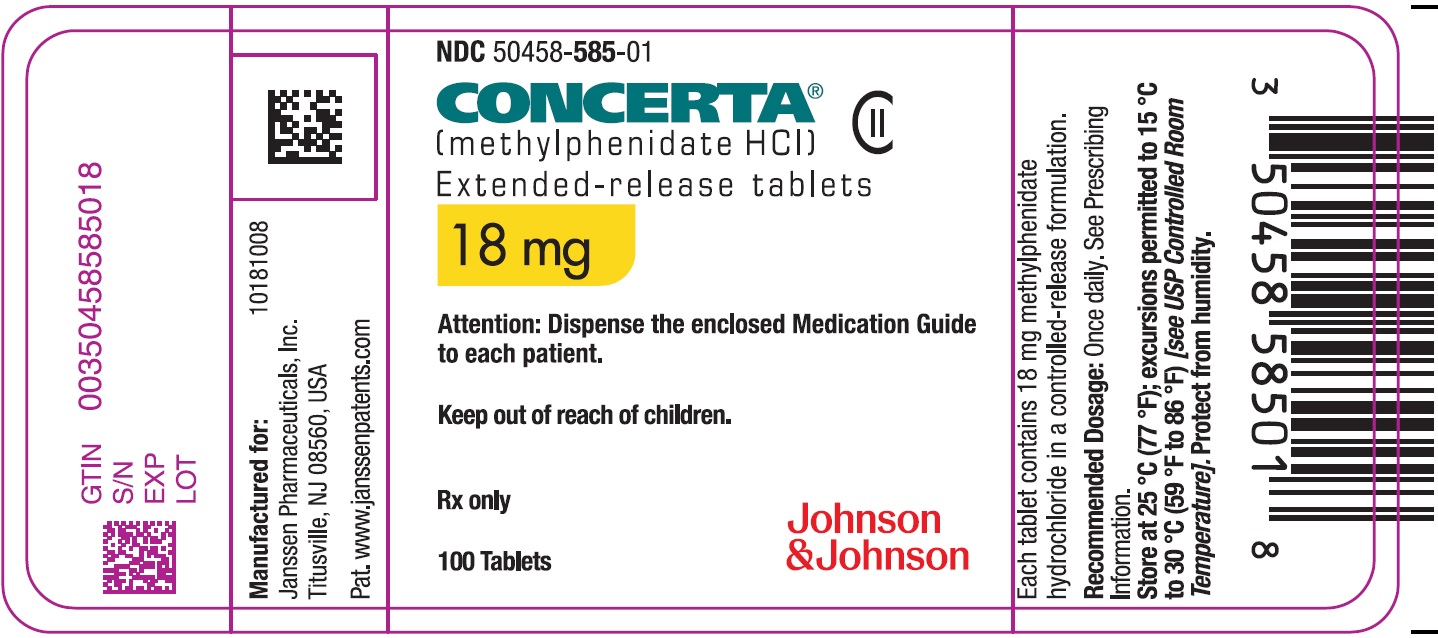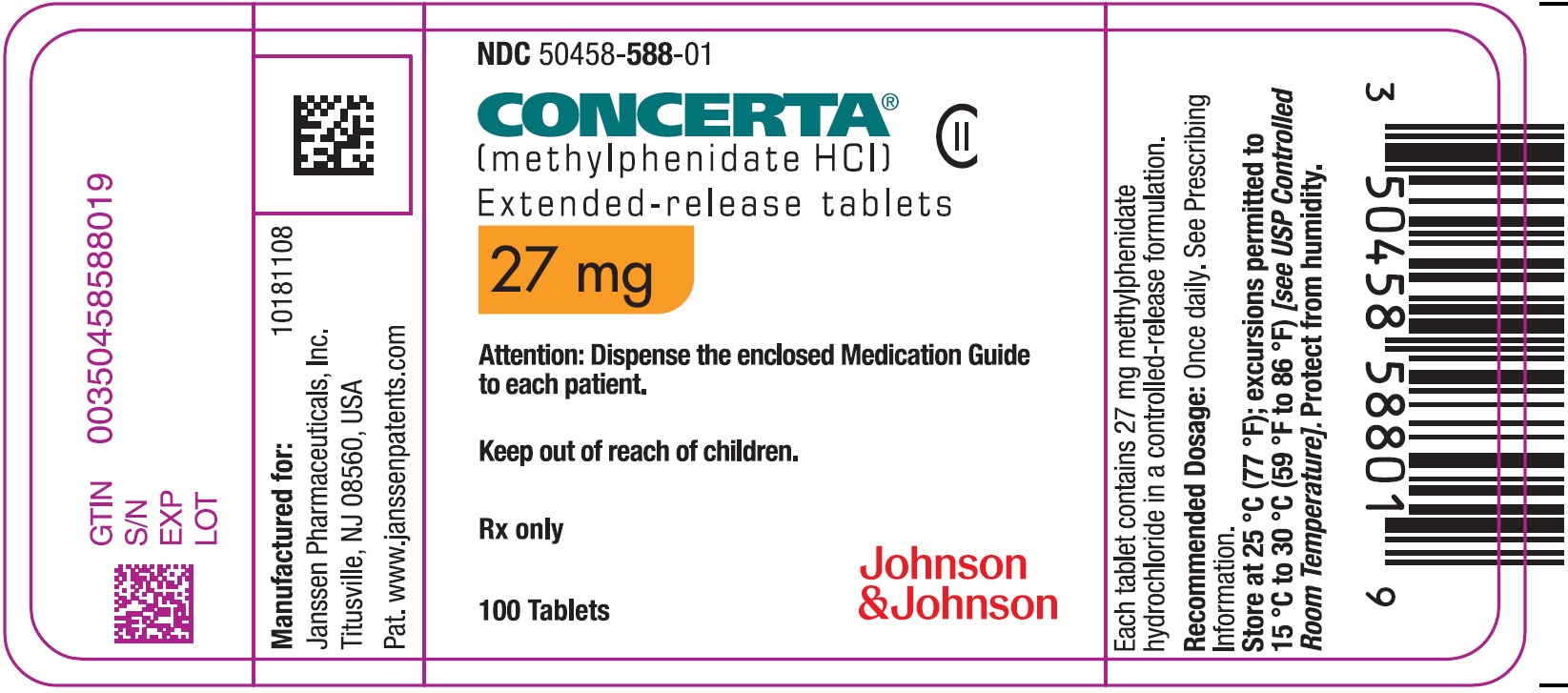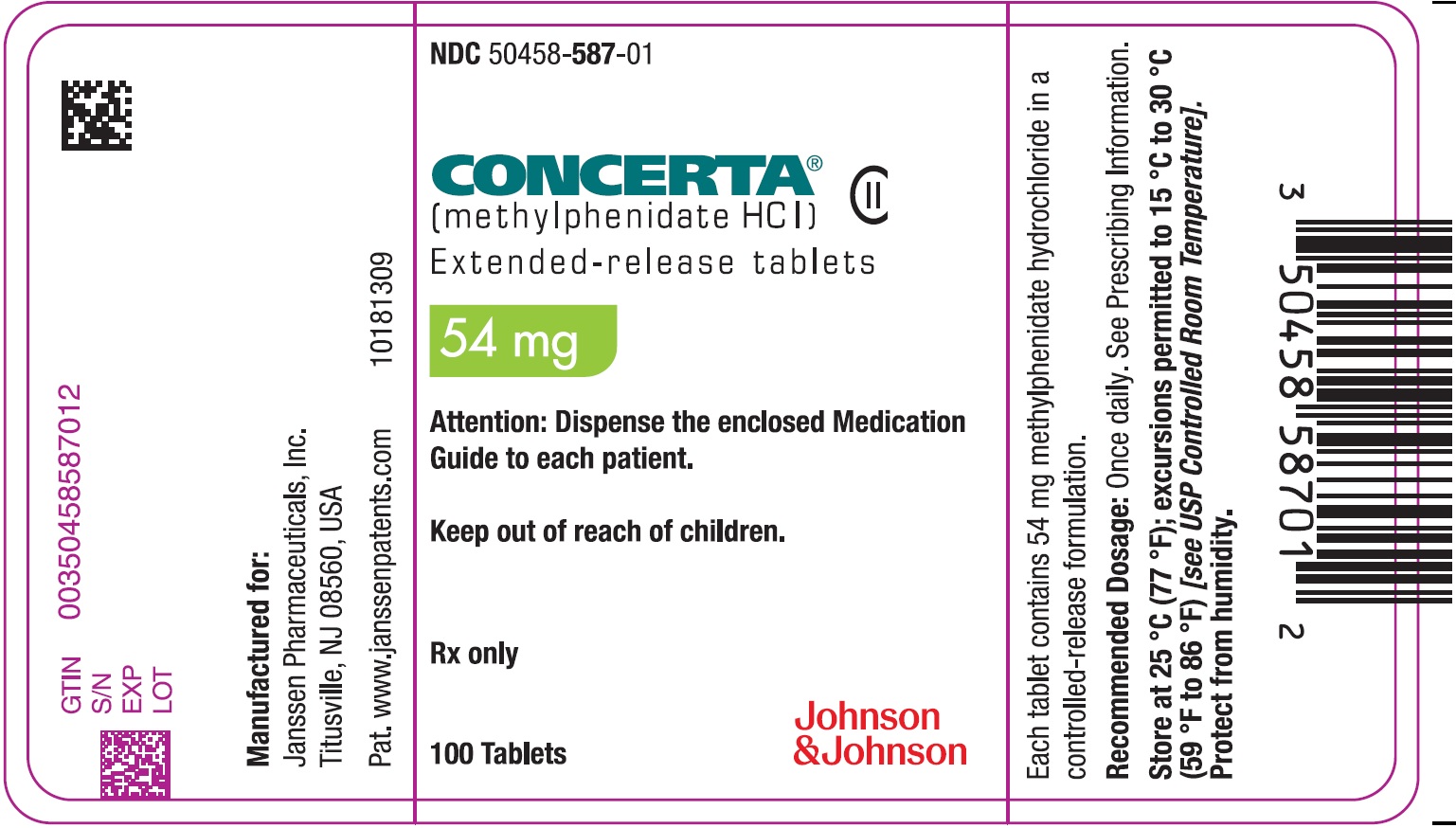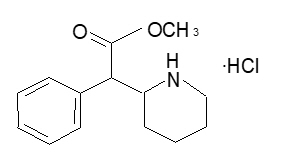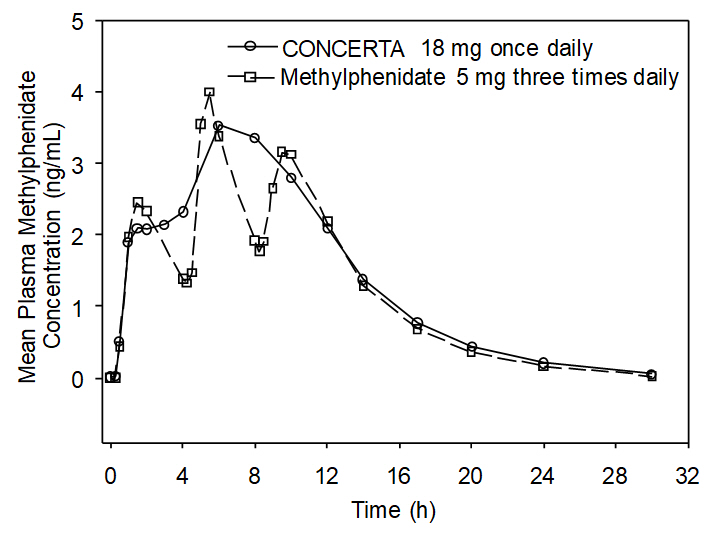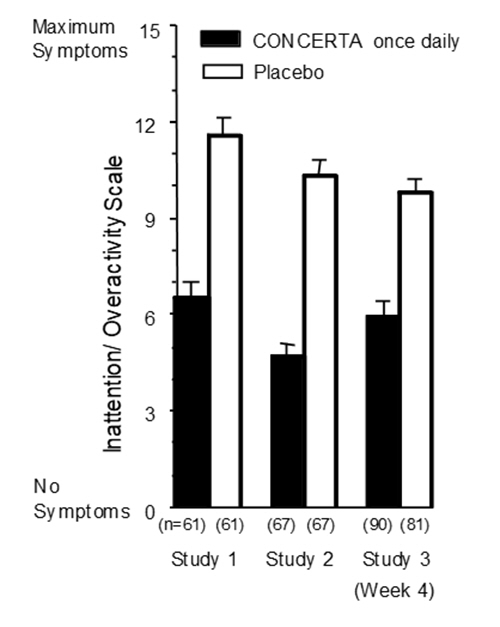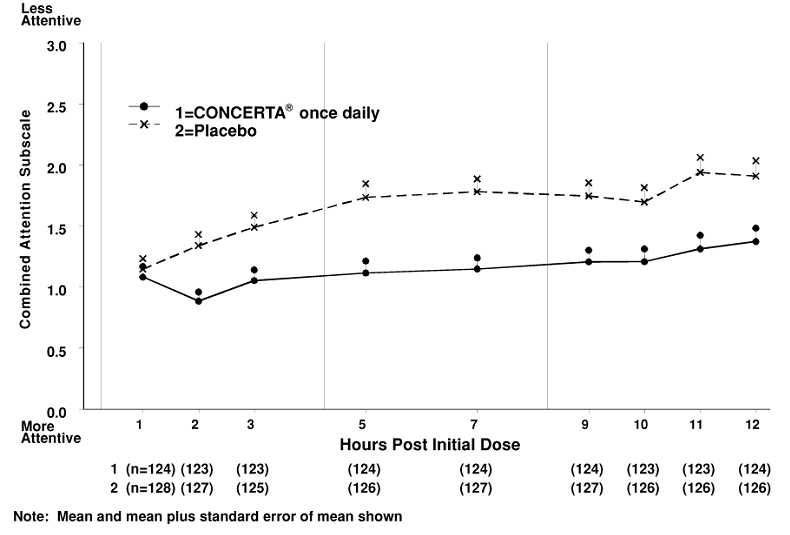 DRUG LABEL: CONCERTA
NDC: 50458-585 | Form: TABLET, EXTENDED RELEASE
Manufacturer: Janssen Pharmaceuticals, Inc.
Category: prescription | Type: HUMAN PRESCRIPTION DRUG LABEL
Date: 20260227
DEA Schedule: CII

ACTIVE INGREDIENTS: METHYLPHENIDATE HYDROCHLORIDE 18 mg/1 1
INACTIVE INGREDIENTS: BUTYLATED HYDROXYTOLUENE; CARNAUBA WAX; HYPROMELLOSE, UNSPECIFIED; LACTOSE, UNSPECIFIED FORM; PHOSPHORIC ACID; POLYETHYLENE GLYCOL, UNSPECIFIED; POVIDONE, UNSPECIFIED; PROPYLENE GLYCOL; SODIUM CHLORIDE; STEARIC ACID; SUCCINIC ACID; FERROSOFERRIC OXIDE; TITANIUM DIOXIDE; TRIACETIN; CELLULOSE ACETATE

HIGHLIGHTS OF PRESCRIBING INFORMATION

These highlights do not include all the information needed to use CONCERTA safely and effectively. See full prescribing information for CONCERTA.
CONCERTA® (methylphenidate hydrochloride) extended-release tablets, for oral use, CII
Initial U.S. Approval: 2000

WARNING: ABUSE, MISUSE, AND ADDICTION

See full prescribing information for complete boxed warning.

CONCERTA has a high potential for abuse and misuse, which can lead to the development of a substance use disorder, including addiction. Misuse and abuse of CNS stimulants, including CONCERTA, can result in overdose and death (5.1, 9.2, 10):

- Before prescribing CONCERTA, assess each patient's risk for abuse, misuse, and addiction.
- Educate patients and their families about these risks, proper storage of CONCERTA, and proper disposal of any unused drug.
- Throughout treatment, reassess each patient's risk and frequently monitor for signs and symptoms of abuse, misuse, and addiction.

RECENT MAJOR CHANGES

Indications and Usage (1) | 9/2025
Dosage and Administration (2.3, 2.4) | 2/2026
Warnings and Precautions: Long-Term Suppression of Growth in Pediatric Patients | 9/2025
Warnings and Precautions: Removal Seizures and Hematologic Monitoring | 2/2026

1 INDICATIONS AND USAGE

CONCERTA is a CNS stimulant indicated for the treatment of attention deficit hyperactivity disorder (ADHD) in patients aged 6 to 65 years old. (1)

Limitations of Use

The use of CONCERTA is not recommended in pediatric patients younger than 6 years of age because they had higher plasma exposure and a higher incidence of adverse reactions (e.g., weight loss) than patients 6 years and older at the same dosage (5.7, 8.4).

2 DOSAGE AND ADMINISTRATION

- Prior to initiating CONCERTA treatment assess for (2.1):
  - the presence of cardiac disease
  - for family history of tics or Tourette' syndrome and clinically evaluate patients for motor or verbal tics or Tourette's syndrome
- Administer once daily in the morning with or without food. Swallow whole with liquids; do not chew, divide, or crush. (2.2)
- Recommended dosage in pediatric patients 6 to 17 years of age new to methylphenidate: starting dosage is18 mg once daily. May be increased weekly in 18 mg increments.
  Maximum dosage for pediatric patients (2.3):
  - 6 to 12 years: 54 mg once daily
  - 13 to 17 years: 72 mg once daily
- Recommended dosage in adults (up to 65 years of age) new to methylphenidate: starting dosage is 18 mg or 36 mg once daily. May be increased weekly in 18 mg increments, up to 72 mg once daily. (2.3)
- Patients currently using immediate-release methylphenidate: starting CONCERTA dosage is based on current dosage regimen. (2.4)

3 DOSAGE FORMS AND STRENGTHS

Extended-release tablets: 18, 27, 36, and 54 mg (3)

4 CONTRAINDICATIONS

- Known hypersensitivity to methylphenidate or other components of CONCERTA (4)
- Receiving concomitant monoamine oxidase inhibitors and within 14 days following discontinuation of treatment with a MAO inhibitor (4)

5 WARNINGS AND PRECAUTIONS

- Risks to Patients with Serious Cardiac Disease: Avoid use in patients with known structural cardiac abnormalities, cardiomyopathy, serious cardiac arrhythmias, coronary artery disease, or other serious cardiac disease (5.2).
- Increased Blood Pressure and Heart Rate: Monitor blood pressure and pulse (5.3).
- Psychiatric Adverse Reactions: Prior to initiating CONCERTA, screen patients for risk factors for developing a manic episode. If new psychotic or manic symptoms occur, consider discontinuing CONCERTA. (5.4)
- Priapism: If abnormally sustained or frequent and painful erections occur, patients should seek immediate medical attention (5.5)
- Peripheral Vasculopathy, including Raynaud's Phenomenon: Carefully assess for digital changes during CONCERTA treatment. Further clinical evaluation (e.g., rheumatology referral) may be appropriate for patients who develop signs or symptoms of peripheral vasculopathy (5.6)
- Long-Term Suppression of Growth in Pediatric Patients: Closely monitor growth (height and weight) in pediatric patients. Pediatric patients not growing or gaining height or weight as expected may need to have their CONCERTA treatment interrupted. (5.7)
- Risk of Gastrointestinal (GI) Obstruction in Patients with GI Narrowing: Only use in patients able to swallow the extended-release tablet whole, and should not ordinarily be used in patients with pre-existing severe GI narrowing. (5.8)
- Acute Angle Closure Glaucoma: CONCERTA-treated patients considered at risk for acute angle closure glaucoma (e.g., patients with significant hyperopia) should be evaluated by an ophthalmologist. (5.9)
- Increased Intraocular Pressure (IOP) and Glaucoma: Prescribe CONCERTA to patients with open-angle glaucoma or abnormally increased IOP only if the benefit of treatment is considered to outweigh the risk. Closely monitor patients with a history of increased IOP or open angle glaucoma. (5.10)
- Motor and Verbal Tics, and Worsening of Tourette's Syndrome: Before initiating CONCERTA, assess the family history and clinically evaluate patients for tics or Tourette's syndrome. Regularly monitor patients for the emergence or worsening of tics or Tourette's syndrome. Discontinue CONCERTA treatment if clinically appropriate. (5.11)

6 ADVERSE REACTIONS

The most common adverse reactions (≥5%) in double-blind clinical trials were:

- Pediatric patients 6 to 17 years: upper abdominal pain. (6.1)
- Adults up to 65 years of age: decreased appetite, headache, dry mouth, nausea, insomnia, anxiety, dizziness, weight decreased, irritability, tachycardia, and hyperhidrosis. (6.1)

To report SUSPECTED ADVERSE REACTIONS, contact Janssen Pharmaceuticals, Inc. at 1-800-JANSSEN (1-800-526-7736) or FDA at 1-800-FDA-1088 or www.fda.gov/medwatch.

7 DRUG INTERACTIONS

- Antihypertensive drugs: Monitor blood pressure. Adjust dosage of antihypertensive drug as needed. (7)
- See additional clinically significant drug interactions, in the DRUG INTERACTIONS section (7).

8 USE IN SPECIFIC POPULATIONS

- Caution should be exercised if administered to nursing mothers (8.3)
- Safety and efficacy has not been established in children less than six years old or elderly patients greater than 65 years of age (8.4 and 8.5)

FULL PRESCRIBING INFORMATION

WARNING: ABUSE, MISUSE, AND ADDICTION

CONCERTA has a high potential for abuse and misuse, which can lead to the development of a substance use disorder, including addiction. Misuse and abuse of CNS stimulants, including CONCERTA, can result in overdose and death [see Overdosage (10)], and this risk is increased with a higher dosage or unapproved methods of administration, such as snorting or injection.

Before prescribing CONCERTA, assess each patient's risk for abuse, misuse, and addiction. Educate patients and their families about these risks, proper storage of CONCERTA, and proper disposal of any unused drug. Throughout CONCERTA treatment, reassess each patient's risk of abuse, misuse, and addiction and frequently monitor for signs and symptoms of abuse, misuse, and addiction [see Warnings and Precautions (5.1) and Drug Abuse and Dependence (9.1, 9.2)].

1 INDICATIONS AND USAGE

CONCERTA is indicated for the treatment of attention deficit hyperactivity disorder (ADHD) in patients aged 6 to 65 years old.

Limitations of Use

The use of CONCERTA is not recommended in pediatric patients younger than 6 years of age because they had higher plasma exposure and a higher incidence of adverse reactions (e.g., weight loss) than patients 6 years and older at the same dosage [see Warnings and Precautions (5.7) and Use in Specific Populations (8.4)].

2 DOSAGE AND ADMINISTRATION

2.1 Pretreatment Screening

Prior to treating patients with CONCERTA, assess:

- For the presence of cardiac disease (e.g., perform a careful history, family history of sudden death or ventricular arrhythmia, and physical exam) [see Warnings and Precautions (5.2)].
- The family history for tics or Tourette' syndrome and clinically evaluate patients for motor or verbal tics or Tourette's syndrome [see Warnings and Precautions (5.11)].

2.2 Important Administration Instructions

Administer CONCERTA orally once daily in the morning with or without food.

Swallow CONCERTA whole with liquids. Do not split, crush, or chew the extended-release tablets because doing so will compromise the extended-release characteristics of CONCERTA and may compromise the effectiveness or safety of CONCERTA.

2.3 Recommended CONCERTA Dosage in Patients New to Methylphenidate

See Table 1 for the recommended once-daily dosage of CONCERTA in patients who were not taking a methylphenidate product. In patients who have not achieved an optimal response at a lower dosage, increase the CONCERTA dosage in 18 mg increments at weekly intervals. However, if a slower titration is recommended for patients who have not achieved an optimal response taking 18 mg of CONCERTA once daily, increase their daily dosage to 27 mg once per day.

Table 1: Recommended CONCERTA Dosage in Patients New to Methylphenidate
Patient Population | Recommended Starting Dosage | Dosage Range
Pediatric patients 6 to 12 years of age | 18 mg once daily | 18 mg to 54 mg once daily
Pediatric patients 13 to 17 years of age | 18 mg once daily | 18 mg to 72 mg once daily (not to exceed 2 mg/kg/day)
Adults 18 to 65 years of age | 18 or 36 mg once daily | 18 mg to 72 mg once daily

2.4 Recommended CONCERTA Dosage in Patients Switching from Another Methylphenidate Product

See Table 2 for the recommended starting dosage of CONCERTA in patients switching from an immediate-release methylphenidate product administered twice daily or three times daily (total daily dosage of 10 to 60 mg/day).

Table 2: Recommended Starting Dosage in Patients Switching from Another Methylphenidate Product
Previous Immediate-release Methylphenidate Daily Dosage | Recommended CONCERTA Starting Dosage
5 mg twice daily or three times daily | 18 mg every morning
10 mg twice daily or three times daily | 36 mg every morning
15 mg twice daily or three times daily | 54 mg every morning
20 mg twice daily or three times daily | 72 mg every morning [Only for patients 13–65 years of age.]

In patients who have not achieved an optimal response at a lower dosage, increase the CONCERTA dosage in 18 mg increments at weekly intervals. The maximum recommended dosage in pediatric patients 6 to 12 years of age is 54 mg/day, and the maximum recommended dosage in patients 13–65 years old is 72 mg/day.

2.5 Dosage Reduction and Discontinuation

If paradoxical aggravation of ADHD symptoms or CONCERTA-associated adverse reactions occur, reduce the CONCERTA dosage or, if necessary, discontinue CONCERTA.

If ADHD improvement is not observed after appropriate dosage modification over a one-month period, discontinue CONCERTA.

3 DOSAGE FORMS AND STRENGTHS

Extended-Release Tablets:

- 18 mg: yellow, imprinted with "alza 18"
- 27 mg: gray, imprinted with "alza 27"
- 36 mg: white, imprinted with "alza 36"
- 54 mg: brownish-red, imprinted with "alza 54"

4 CONTRAINDICATIONS

CONCERTA is contraindicated in patients:

- Known to be hypersensitive to methylphenidate or other components of CONCERTA. Hypersensitivity reactions, such as angioedema and anaphylactic reactions, have been reported in patients treated with CONCERTA. [see Adverse Reactions (6)].
- Receiving concomitant monoamine oxidase inhibitors (MAOIs), and within 14 days following discontinuation of treatment with a MAO inhibitor because of the risk of a hypertensive crisis [see Drug Interactions (7)].

5 WARNINGS AND PRECAUTIONS

5.1 Abuse, Misuse, and Addiction

CONCERTA has a high potential for abuse and misuse. The use of CONCERTA exposes individuals to the risks of abuse and misuse, which can lead to the development of a substance use disorder, including addiction [see Drug Abuse and Dependence (9.1, 9.2)]. Misuse and abuse of CNS stimulants, including CONCERTA, can result in overdose and death [see Overdosage (10)], and this risk is increased with higher dosage or unapproved methods of administration, such as snorting or injection.

Before prescribing CONCERTA, assess each patient's risk for abuse, misuse, and addiction. Educate patients and their families about these risks and proper disposal of any unused drug. Advise patients to store CONCERTA in a safe place, preferably locked, and instruct patients to not give CONCERTA to anyone else. Throughout CONCERTA treatment, reassess each patient's risk of abuse, misuse, and addiction and frequently monitor for signs and symptoms of abuse, misuse, and addiction.

5.2 Risks to Patients with Serious Cardiac Disease

Sudden death has been reported in patients with structural cardiac abnormalities or other serious cardiac disease who were treated with CNS stimulants at the recommended ADHD dosage.

Avoid CONCERTA use in patients with known structural cardiac abnormalities, cardiomyopathy, serious cardiac arrhythmia, coronary artery disease, or other serious cardiac disease.

5.3 Increased Blood Pressure and Heart Rate

CNS stimulants may cause an increase in blood pressure (mean increase approximately 2 to 4 mm Hg) and heart rate (mean increase approximately 3 to 6 beats per minute) [see Adverse Reactions (6)]. Some patients may have larger increases.

Monitor all CONCERTA-treated patients for hypertension and tachycardia.

5.4 Psychiatric Adverse Reactions

Exacerbation of Psychosis in Patients with a Psychotic Disorder

CNS stimulants, including CONCERTA, may exacerbate behavior disturbance and thought disorder in patients with a pre-existing psychotic disorder.

Induction of a Manic Episode in Patients with Bipolar Disorder

CNS stimulants, including CONCERTA, may induce a manic or mixed episode in patients with bipolar disorder. Prior to initiating CONCERTA treatment, screen patients for risk factors for developing a manic episode (e.g., history of depressive symptoms or a family history of suicide, bipolar disorder, or depression).

New Psychotic or Manic Symptoms in Patients without a History of a Bipolar or Psychotic Disorder

CNS stimulants (including CONCERTA), at the recommended dosage, may cause psychotic or manic symptoms (e.g., hallucinations, delusional thinking, or mania) in patients without a prior history of psychotic illness or mania. In a pooled analysis of multiple short-term, placebo-controlled studies of CNS stimulants, psychotic or manic symptoms occurred in approximately 0.1% of CNS stimulant-treated patients, compared with 0% of placebo-treated patients. If such symptoms occur, consider discontinuing CONCERTA.

5.5 Priapism

Prolonged and painful erections, sometimes requiring surgical intervention, have been reported with methylphenidate use in adult and pediatric male patients [see Adverse Reactions (6)]. Although priapism was not reported with methylphenidate initiation, priapism occurred in patients treated with methylphenidate after some time, often subsequent to an increase in dosage. Priapism also occurred during methylphenidate withdrawal (drug holidays or during discontinuation).

CONCERTA-treated patients who develop abnormally sustained or frequent and painful erections should seek immediate medical attention.

5.6 Peripheral Vasculopathy, including Raynaud's Phenomenon

CNS stimulants, including CONCERTA, used to treat ADHD are associated with peripheral vasculopathy, including Raynaud's phenomenon [see Adverse Reactions (6.2)]. Signs and symptoms of these cases of peripheral vasculopathy were usually intermittent and mild; however, sequelae have included digital ulceration and/or soft tissue breakdown. Effects of peripheral vasculopathy, including Raynaud's phenomenon, were observed in post-marketing reports and at the therapeutic dosages of CNS stimulants in all age groups throughout the course of treatment. Signs and symptoms of peripheral vasculopathy generally improved after CNS stimulant dosage reduction or discontinuation.

During CONCERTA treatment, carefully assess for digital changes. Further clinical evaluation (e.g., rheumatology referral) may be appropriate for CONCERTA-treated patients who develop signs or symptoms of peripheral vasculopathy.

5.7 Long-Term Suppression of Growth in Pediatric Patients

CONCERTA is not approved for use and is not recommended in pediatric patients below 6 years of age [see Use in Specific Populations (8.4)]. CNS stimulants have been associated with weight loss and slowing of growth rate in pediatric patients.

Pediatric patients 7 to 13 years of age who received methylphenidate for 7 days per week for over 14 months to over 36 months had a temporary slowing in growth rate (on average, a total of about 2 cm less growth in height and 2.7 kg less growth in weight over 3 years), without evidence of growth rebound during this development period.

Closely monitor growth (weight and height) in CONCERTA-treated pediatric patients. Pediatric patients who are not growing or gaining height or weight as expected may need to have their treatment interrupted.

5.8 Risk of Gastrointestinal Obstruction in Patients with Gastrointestinal Narrowing

Because CONCERTA extended-release tablets are nondeformable and do not appreciably change in shape in the gastrointestinal (GI) tract, CONCERTA should not ordinarily be administered to patients with pre-existing severe pathologic or iatrogenic GI narrowing. There have been rare reports of obstructive GI symptoms in patients with known strictures in association with the ingestion of drugs in nondeformable modified-release dosage forms.

CONCERTA should be used only in patients who are able to swallow the extended-release tablets whole [see Dosage and Administration (2.2)].

5.9 Acute Angle Closure Glaucoma

There have been reports of angle closure glaucoma associated with methylphenidate treatment.

Although the mechanism is not clear, CONCERTA-treated patients considered at risk for acute angle closure glaucoma (e.g., patients with significant hyperopia) should be evaluated by an ophthalmologist.

5.10 Increased Intraocular Pressure and Glaucoma

There have been reports of an elevation of intraocular pressure (IOP) associated with methylphenidate treatment [see Adverse Reactions (6)].

Prescribe CONCERTA to patients with open-angle glaucoma or abnormally increased IOP only if the benefit of treatment is considered to outweigh the risk. Closely monitor CONCERTA-treated patients with a history of abnormally increased IOP or open angle glaucoma.

5.11 Motor and Verbal Tics, and Worsening of Tourette's Syndrome

CNS stimulants, including methylphenidate, have been associated with the onset or exacerbation of motor and verbal tics [see Adverse Reactions (6)]. Worsening of Tourette's syndrome has also been reported.

Before initiating CONCERTA, assess the family history for tics or Tourette' syndrome and clinically evaluate patients for tics or Tourette's syndrome. Regularly monitor CONCERTA-treated patients for the emergence or worsening of tics or Tourette's syndrome, and discontinue CONCERTA treatment if clinically appropriate.

6 ADVERSE REACTIONS

The following are discussed in more detail in other sections of the labeling:

- Abuse, Misuse, and Addiction [see Boxed Warning, Warnings and Precautions (5.1), Drug Abuse and Dependence (9.2)]
- Hypersensitivity Reactions [see Contraindications (4)]
- Monoamine Oxidase Inhibitors [see Contraindications (4), Drug Interactions (7)]
- Risks to Patients with Serious Cardiac Disease [see Warnings and Precautions (5.2)]
- Increased Blood Pressure and Heart Rate [see Warnings and Precautions (5.3)]
- Psychiatric Adverse Reactions [see Warnings and Precautions (5.4)]
- Priapism [see Warnings and Precautions (5.5)]
- Peripheral Vasculopathy, including Raynaud's Phenomenon [see Warnings and Precautions (5.6)]
- Long-Term Suppression of Growth in Pediatric Patients [see Warnings and Precautions (5.7)]
- Risks of Gastrointestinal Obstruction in Patients with Gastrointestinal Narrowing [see Warnings and Precautions (5.8)]
- Acute Angle Closure Glaucoma [see Warnings and Precautions (5.9)]
- Increased Intraocular Pressure and Glaucoma [see Warnings and Precautions (5.10)]
- Motor and Verbal Tics, and Worsening of Tourette's Syndrome [see Warnings and Precautions (5.11)]

6.1 Clinical Trial Experience

Because clinical trials are conducted under widely varying conditions, adverse reaction rates observed in the clinical trials of a drug cannot be directly compared to rates in clinical trials of another drug and may not reflect the rates observed in clinical practice. The data below is based on a total of 3,906 patients in clinical studies who received CONCERTA. Patients aged 6 up to 65 years old with ADHD were evaluated in 6 controlled clinical studies and 11 open-label clinical studies [see Table 3].

Table 3: CONCERTA-treated Patients in Double-Blind and Open-Label Clinical Studies
Patient Population | N | Dosage Range
Pediatric patients 6 to 12 years of age | 2,216 | 18 to 54 mg once daily
Adolescents | 502 | 18 to 72 mg once daily
Adults up to 65 years of age | 1,188 | 18 to 108 mg once daily

The most common adverse reactions (≥5%) in double-blind clinical trials were:

- Pediatric patients: upper abdominal pain [see Table 4].
- Adults: decreased appetite, headache, dry mouth, nausea, insomnia, anxiety, dizziness, weight decreased, irritability, tachycardia, and hyperhidrosis [see Table 5].

The most common adverse reactions associated with CONCERTA discontinuation (≥1%) from the pediatric and adult clinical trials were anxiety, irritability, insomnia, and increased blood pressure.

Most Common Adverse Reactions in Double-Blind, Placebo-Controlled Clinical Trials: Adverse reactions in either the pediatric or adult double-blind adverse reactions tables may be relevant for both patient populations.

Adverse Reactions in Pediatric Patients Aged 6 years and Older

Table 4 displays adverse reactions reported in 2% or more of CONCERTA-treated pediatric patients ages 6 and older with ADHD in 4 placebo-controlled, double-blind clinical trials.

Table 4: Most Common Adverse Reactions [Reported in ≥ 2% of CONCERTA-treated patients] in Pediatric Patients 6 Years of Age and Older with ADHD in 4 Placebo-Controlled, Double-Blind Clinical Trials
 | CONCERTA (n=321) | Placebo (n=318)
Upper abdominal pain | 6% | 4%
Insomnia [Initial insomnia (CONCERTA=0.6%) and insomnia (CONCERTA=2.2%) terms were combined into Insomnia.] | 3% | 1%
Nasopharyngitis | 3% | 2%
Vomiting | 3% | 2%
Pyrexia | 2% | 1%

Adverse Reactions in Adults

Table 5 lists the adverse reactions reported in 2% or more of CONCERTA-treated adults with ADHD in 2 placebo-controlled, double-blind clinical trials.

Table 5: Most Common Adverse Reactions [Reported in ≥ 2% of CONCERTA-treated patients] in Adults with ADHD in 2 Placebo-Controlled, Double-Blind Clinical Trials
 | CONCERTA [Included dosages up to 108 mg/day (1.5 times the maximum recommended dosage).] (n=415) | Placebo (n=212)
Decreased appetite | 25% | 7%
Headache | 22% | 16%
Dry mouth | 14% | 4%
Nausea | 13% | 3%
Insomnia | 12% | 6%
Anxiety | 8% | 2%
Decreased weight | 7% | 3%
Dizziness | 7% | 5%
Irritability | 6% | 1%
Tachycardia | 5% | 0%
Hyperhidrosis | 5% | 1%
Depressed mood | 4% | 1%
Initial insomnia | 4% | 3%
Restlessness | 3% | 0%
Palpitations | 3% | 1%
Nervousness | 3% | 1%
Tremor | 3% | 1%
Upper respiratory tract infection | 2% | 1%
Agitation | 2% | 1%
Dyspepsia | 2% | 1%

Other Adverse Reactions Observed in Clinical Trials of CONCERTA

The following adverse reactions occurred in less than 2% of CONCERTA-treated patients ages 6 to 65 years of age in the double-blind and open-label clinical ADHD trials.

- Blood and Lymphatic System Disorders: Leukopenia
- Cardiac Disorders: Cardiac murmur, Hypertension, Heart rate increased
- Ear and Labyrinth Disorders: Vertigo
- Eye Disorders: Accommodation disorder, Dry eye, Vision blurred
- Gastrointestinal Disorders: Abdominal discomfort/pain, Constipation, Diarrhea, Vomiting
- General Disorders and Administration Site Conditions: Asthenia, Fatigue, Feeling jittery, Thirst
- Hepatobiliary Disorders: Hepatic enzymes increased
- Infections and Infestations: Sinusitis
- Metabolism and Nutrition Disorders: Anorexia
- Musculoskeletal and Connective Tissue Disorders: Muscle spasms, Muscle tightness
- Nervous System Disorders: Lethargy, Paresthesia, Psychomotor hyperactivity, Sedation, Somnolence, Tension headache
- Psychiatric Disorders: Affect lability, Aggression, Anger, Bruxism, Confusional state, Depression, Hypervigilance, decreased libido, Mood swings, Panic attack, Sleep disorder, Tearfulness, Tension, Tic
- Reproductive System and Breast Disorders: Erectile dysfunction
- Respiratory, Thoracic and Mediastinal Disorders: Cough, Dyspnea, Oropharyngeal pain
- Skin and Subcutaneous Tissue Disorders: Rash
- Vascular Disorders: Hot flush

Discontinuation Due to Adverse Reactions

In the 2 placebo-controlled studies in adults with ADHD, 25 (6%) CONCERTA-treated patients and 6 (3%) placebo-treated patients discontinued due to an adverse reaction. In the CONCERTA group, adverse reactions leading to discontinuation with an incidence of >0.5% were anxiety (1.7%), irritability (1.4%), increased blood pressure (1%), and nervousness (0.7%). In the placebo group, adverse reactions leading to discontinuation with an incidence of >0.5% were increased blood pressure (0.9%) and depressed mood (0.9%).

In the 11 open-label studies in patients 6 to 65 years of age with ADHD, 266 (7%) CONCERTA-treated patients discontinued due to an adverse reaction including insomnia (1.2%), irritability (0.8%), anxiety (0.7%), decreased appetite (0.7%), and tic (0.6%).

Blood Pressure and Heart Rate Increases

- In the 1-week treatment, controlled trials in pediatric patients 6 to 12 years of age with ADHD (Studies 1 and 2) [see Clinical Studies (14.2)], both the CONCERTA once daily group and the methylphenidate three times daily group increased resting pulse by an average of 2 to 6 beats per minute (bpm) and increased the average systolic and diastolic blood pressure roughly 1 to 4 mm Hg during the day, relative to placebo.
- In the randomized withdrawal portion of the double-blind, placebo-controlled trial with pediatric patients 13 to 17 years of age with ADHD (Study 4) [see Clinical Studies (14.3)], mean increases from baseline in resting pulse rate were observed with CONCERTA and placebo at the end of the double-blind phase (5 and 3 beats/minute (bpm), respectively). At the end of four weeks of treatment, mean increases from baseline in blood pressure for CONCERTA and placebo-treated patients were 0.7 and 0.7 mm Hg (systolic) and 2.6 and 1.4 mm Hg (diastolic), respectively.
- In the 7-week dose-titration, placebo-controlled study in adults 18 to 65 years of age with ADHD (Study 5) [see Clinical Studies (14.4)], mean changes from baseline in resting pulse rate were 3.6 in CONCERTA-treated patients and -1.6 for placebo-treated patients after 7 weeks of treatment. Mean changes from baseline in blood pressure after 7 weeks of treatment in CONCERTA-treated and placebo-treated patients were –1.2 and –0.5 mm Hg (systolic) and 1.1 and 0.4 mm Hg (diastolic), respectively [see Warnings and Precautions (5.3)].
- In the 5-week fixed-dose, placebo-controlled trial in adults 18 to 65 years of age with ADHD (Study 5) [see Clinical Studies (14.4)], dose-dependent mean increases of 3.9 to 9.8 bpm from baseline in standing pulse rate were observed with CONCERTA-treated patients and 2.7 bpm with placebo-treated patients at the end of 5 weeks. Mean changes from baseline in standing blood pressure after 5 weeks of treatment ranged from 0.1 to 2.2 mm Hg (systolic) and -0.7 to 2.2 mm Hg (diastolic) for CONCERTA-treated patients and 1.1 mm Hg (systolic) and -1.8 mm Hg (diastolic) for placebo-treated patients.

6.2 Postmarketing Experience

The following adverse reactions have been identified during post-approval use of CONCERTA. Because these reactions are reported voluntarily from a population of uncertain size, it is not always possible to reliably estimate their frequency:

- Blood and Lymphatic System Disorders: Pancytopenia, Thrombocytopenia, Thrombocytopenic purpura
- Cardiac Disorders: Angina pectoris, Bradycardia, Supraventricular tachycardia, Ventricular extrasystoles
- Eye Disorders: Diplopia, Increased intraocular pressure, Mydriasis
- General Disorders and Administration Site Conditions: Chest pain, Drug effect decreased, Hyperpyrexia
- Hepatobiliary Disorders: Hepatocellular injury, Acute hepatic failure, Blood bilirubin increased
- Immune System Disorders: Hypersensitivity reactions such as Angioedema, Anaphylactic reactions, Auricular swelling, Exanthemas NEC
- Investigations: Blood alkaline phosphatase increased, Platelet count decreased,
- Musculoskeletal and Connective Tissue Disorders: Arthralgia, Myalgia, Muscle twitching, Rhabdomyolysis
- Nervous System Disorders: Convulsion, Grand mal convulsion, Stroke in pediatric patients, Dyskinesia, Serotonin syndrome in combination with serotonergic drugs, Motor and Verbal Tics
- Psychiatric Disorders: Disorientation, Hallucination, Mania, Logorrhea
- Reproductive System and Breast Disorders: Priapism
- Skin and Subcutaneous Tissue Disorders: Alopecia, Bullous conditions, Erythema, Exfoliative conditions, Pruritus, Urticarias
- Vascular Disorders: Raynaud's phenomenon

7 DRUG INTERACTIONS

Table 6 describes clinically significant drug interactions with CONCERTA.

Table 6: Clinically Significant Drug Interactions
Monoamine Oxidase Inhibitors
Prevention or Management | Concomitant use of CNS stimulants, including CONCERTA, with MAOIs or within 14 days after discontinuing an MAOI is contraindicated [see Contraindications (4)].
Mechanism and Clinical Effect(s) | Concomitant use of MAOIs and CNS stimulants, including CONCERTA, can cause hypertensive crisis. Potential outcomes include death, stroke, myocardial infarction, aortic dissection, ophthalmological complications, eclampsia, pulmonary edema, and renal failure.
Antihypertensive Drugs
Prevention or Management | Increase monitoring for blood pressure and adjust the dosage of the antihypertensive drug, as needed.
Mechanism and Clinical Effect(s) | CONCERTA may decrease effectiveness of drugs used to treat hypertension [see Warnings and Precautions 5.3].
Halogenated Anesthetics
Prevention or Management | Avoid use of CONCERTA in patients being treated with anesthetics on the day of surgery.
Mechanism and Clinical Effect(s) | Concomitant use of halogenated anesthetics and CONCERTA may increase the risk of sudden blood pressure and heart rate increase during surgery.
Risperidone
Prevention or Management | Monitor for signs of extrapyramidal symptoms.
Mechanism and Clinical Effect(s) | The risk of risperidone-associated extrapyramidal symptoms may increase in patients taking concomitant CONCERTA when there is a change in the CONCERTA or risperidone dosage.

8 USE IN SPECIFIC POPULATIONS

8.1 Pregnancy

Pregnancy Exposure Registry

There is a pregnancy exposure registry that monitors pregnancy outcomes in women exposed to ADHD drugs, including CONCERTA, during pregnancy. Healthcare providers are encouraged to advise patients to register by calling the National Pregnancy Registry for ADHD Medications at 1-866-961-2388 or visiting https://womensmentalhealth.org/adhd-medications/.

Risk Summary

Published studies and post-marketing reports on methylphenidate use during pregnancy have inconsistent findings about a drug-associated risk of major birth defects, miscarriage, or adverse maternal or fetal outcomes. There are risks to the fetus associated with the use of central nervous system (CNS) stimulants during pregnancy (see Clinical Considerations).

No effects on morphological development were observed in embryo-fetal development studies with oral administration of methylphenidate to pregnant rats and rabbits throughout organogenesis at doses up to 4 and 16 times, respectively, the maximum recommended human dose (MRHD) of 72 mg/day given to adults on a mg/m^2 basis. However, spina bifida was observed in rabbits at a dose 54 times the MRHD given to adults. A slight decrease in body weight was observed in pregnant rats at the highest dose of 30 mg/kg/day (4 times the MRHD given to adults).

In a pre- and postnatal development study in which rats were treated with oral administration of methylphenidate throughout pregnancy and lactation, a decrease in pup body weight, alterations in sensory and neuromotor performance, and deficits in learning and memory were observed in both sexes at the highest dose (4 times the MRHD given to adults on a mg/m^2 basis) (see Data).

The background risk of major birth defects and miscarriage in those with ADHD is unknown. All pregnancies have a background risk of birth defects, loss, or other adverse outcomes. In the U.S. general population, the estimated background risk of major birth defects and miscarriage in clinically recognized pregnancies is 2% to 4% and 15% to 20%, respectively.

Clinical Considerations

Fetal/Neonatal Adverse Reactions: CNS stimulants, such as CONCERTA, can cause vasoconstriction and thereby decrease placental perfusion. No fetal and/or neonatal adverse reactions have been reported with the use of a therapeutic dosage of methylphenidate during pregnancy; however, premature delivery and low birth weight infants have been reported in amphetamine dependent mothers.

Data

Animal Data: In embryo-fetal development studies conducted in rats and rabbits, methylphenidate was administered orally at doses up to 30 and 200 mg/kg/day, respectively, during the period of organogenesis.

Malformations (increased incidence of fetal spina bifida) were observed in rabbits at the highest dose, which is approximately 54 times the maximum recommended human dose (MRHD) of 72 mg/day given to adults on a mg/m^2 basis. The no effect level for embryo-fetal development in rabbits was 60 mg/kg/day (16 times the MRHD given to adults on a mg/m^2 basis).

There was no evidence of changes in morphological development in rats, although a reduction in maternal body weight was observed at the highest dose of 30 mg/kg/day (4 times the MRHD of 72 mg/day given to adults (on a mg/m^2 basis). The no effect level for maternal body weight in rats is 5 mg/day (equal to the MRHD for adults on a mg/m^2 basis); and the no effect level for embryo-fetal development is 30 mg/kg/day (4 times the MRHD for adults on a mg/m^2 basis).

When methylphenidate was administered to rats throughout pregnancy and lactation at doses of up to 30 mg/kg/day, decreases in offspring body weight, alterations in sensory and neuromotor performance, and deficits in learning and memory were observed in both sexes at the highest dose (4 times the MRHD of 72 mg/day, given to adults on a mg/m^2 basis). The no effect level for pre- and post-natal development in rats was 12.5 mg/kg/day (2 times the MRHD given to adults on a mg/m^2 basis).

8.2 Lactation

Risk Summary

Limited published literature, based on breast milk sampling from a small number of methylphenidate-treated lactating women, reports that methylphenidate is present in human milk, which resulted in infant doses of 0.16% to 0.7% of the maternal weight-adjusted methylphenidate dosage and a milk/plasma ratio ranging between 1.1 and 2.7. There are no reports of adverse effects on the breastfed infant or effects on milk production. Long-term neurodevelopmental effects on infants from CNS stimulant exposure are unknown.

The developmental and health benefits of breastfeeding should be considered along with the mother's clinical need for CONCERTA and any potential adverse effects on the breastfed child from CONCERTA or from the underlying maternal condition.

Clinical Considerations

Monitor breastfeeding infants of CONCERTA-treated lactating women for adverse reactions, such as agitation, insomnia, anorexia, and reduced weight gain.

8.4 Pediatric Use

The safety and effectiveness of CONCERTA for the treatment of ADHD have been established in pediatric patients 6 years of age and older. The safety and effectiveness of CONCERTA have not been established in pediatric patients below the age of 6 years.

In studies evaluating extended-release methylphenidate products, patients 4 to <6 years of age had higher systemic methylphenidate exposures than those observed in older pediatric patients at the same dosage. Pediatric patients 4 to <6 years of age also had a higher incidence of adverse reactions, including weight loss.

CNS stimulants have been associated with weight loss and slowing of growth rate in pediatric patients. Growth (weight and height) should be monitored in pediatric patients during treatment with CNS stimulants, including CONCERTA. Pediatric patients who are not growing or gaining weight as expected may need to have their CONCERTA treatment interrupted [see Warnings and Precautions (5.7)].

Juvenile Animal Toxicity Data

Rats treated with methylphenidate early in the postnatal period through sexual maturation demonstrated a decrease in spontaneous locomotor activity in adulthood. A deficit in acquisition of a specific learning task was observed in females only. The doses at which these findings were observed are at least 4 times the MRHD of 54 mg/day given to pediatric patients 6 to 12 years of age on a mg/m^2 basis.

In a study conducted in young rats, methylphenidate was administered orally at doses of up to 100 mg/kg/day for 9 weeks, starting early in the postnatal period (postnatal Day 7) and continuing through sexual maturity (postnatal Week 10). When these animals were tested as adults (postnatal Weeks 13 to 14), decreased spontaneous locomotor activity was observed in males and females previously treated with 50 mg/kg/day (approximately 4 times the MRHD of 54 mg/day given to pediatric patients 6 to 12 years of age on a mg/m^2 basis) or greater, and a deficit in the acquisition of a specific learning task was seen in females exposed to the highest dose (9 times the MRHD given to pediatric patients 6 to 12 years of age on a mg/m^2 basis). The no effect level for juvenile neurobehavioral development in rats was 5 mg/kg/day (approximately 0.4 times the MRHD given to pediatric patients 6 to 12 years of age on a mg/m^2 basis). The clinical significance of the long-term behavioral effects observed in rats is unknown.

8.5 Geriatric Use

CONCERTA is not indicated for use in patients greater than 65 years of age.

9 DRUG ABUSE AND DEPENDENCE

9.1 Controlled Substance

CONCERTA contains methylphenidate, a Schedule II controlled substance.

9.2 Abuse

CONCERTA has a high potential for abuse and misuse which can lead to the development of a substance use disorder, including addiction [see Warnings and Precautions (5.1)].

Abuse is the intentional non-therapeutic use of a drug, even once, to achieve a desired psychological or physiological effect. Misuse is the intentional use, for therapeutic purposes, of a drug by an individual in a way other than prescribed by a health care provider or for whom it was not prescribed. Drug addiction is a cluster of behavioral, cognitive, and physiological phenomena that may include a strong desire to take the drug, difficulties in controlling drug use (e.g., continuing drug use despite harmful consequences, giving a higher priority to drug use than other activities and obligations), and possible tolerance or physical dependence.

Misuse and abuse of CONCERTA may cause increased heart rate, respiratory rate, or blood pressure; sweating; dilated pupils; hyperactivity; restlessness; insomnia; decreased appetite; loss of coordination; tremors; flushed skin; vomiting; and/or abdominal pain. Anxiety, psychosis, hostility, aggression, and suicidal or homicidal ideation have also been observed with CNS stimulants abuse and/or misuse. Misuse and abuse of CNS stimulants, including CONCERTA, can result in overdose and death [see Overdosage (10)], and this risk is increased with higher doses or unapproved methods of administration, such as snorting or injection.

Studies of Abuse Potential with CONCERTA

In two placebo- and active-controlled, crossover human abuse potential (HAP) studies, the relative abuse potential of single oral doses of CONCERTA were compared to single oral doses of immediate-release methylphenidate (IR MPH) and placebo in subjects with a history of recreational CNS stimulant use. In these studies, the response for each of the abuse-related subjective measures was defined as the maximum effect within the first 8 hours after treatment administration. When evaluating these results, consider that 22% of the total methylphenidate amount in CONCERTA (methylphenidate hydrochloride) extended-release tablets is available for immediate release and the remaining 78% is available for extended-release over 24 hours.

- In the first HAP study (n=40), single dose administration of CONCERTA 108 mg (1.5 times the maximum recommended adult dose of CONCERTA), IR MPH 60 mg (2 times the maximum recommended adult dose of IR MPH), or placebo were administered to subjects in a cross-over design. CONCERTA 108 mg and IR MPH 60 mg produced responses on the subjective measures of Drug Liking and Abuse Potential that were statistically similar, and both were statistically significantly greater than the responses to placebo. However, on subjective measures of Euphoria, CONCERTA 108 mg produced responses that were statistically less than those produced by IR MPH 60 mg.
- In the second HAP study (n=49), a single dose of CONCERTA 108 mg (1.5 times the maximum recommended adult dose of CONCERTA), CONCERTA 54 mg (0.75 times the maximum recommended adult dose of CONCERTA), IR MPH 90 mg (3 times the maximum recommended adult dose of IR MPH), 50 mg (1.7 times the maximum recommended adult dose of IR MPH), or placebo were administered to subjects in a cross-over design. The three active treatments each produced responses on the subjective measure of Drug Liking that were statistically significantly greater than responses to placebo. IR MPH produced greater responses on Drug Liking compared to CONCERTA when similar doses were compared (50 mg vs. 54 mg, and 90 mg vs. 108 mg, respectively), consistent with the extended-release properties of CONCERTA. However, there were no significant differences in response between CONCERTA 108 mg and IR MPH 50 mg on the subjective measures of Drug Liking and Euphoria.

The clinical significance of the differences in response between CONCERTA and IR MPH on subjective measures of abuse potential as reported in these HAP studies is unknown.

9.3 Dependence

Physical Dependence

CONCERTA may produce physical dependence. Physical dependence is a state that develops as a result of physiological adaptation in response to repeated drug use, manifested by withdrawal signs and symptoms after abrupt discontinuation or a significant dose reduction of a drug.

Withdrawal signs and symptoms after abrupt discontinuation or dosage reduction following prolonged use of CNS stimulants including CONCERTA included dysphoric mood; depression; fatigue; vivid, unpleasant dreams; insomnia or hypersomnia; increased appetite; and psychomotor retardation or agitation.

Tolerance

CONCERTA may produce tolerance. Tolerance is a physiological state characterized by a reduced response to a drug after repeated administration (i.e., a higher dose of a drug is required to produce the same effect that was once obtained at a lower dose).

10 OVERDOSAGE

10.1 Clinical Effects of Overdose

Overdose of CNS stimulants is characterized by the following sympathomimetic effects:

- Cardiovascular effects including tachyarrhythmias, and hypertension or hypotension. Vasospasm, myocardial infarction, or aortic dissection may precipitate sudden cardiac death. Takotsubo cardiomyopathy may develop.
- CNS effects including psychomotor agitation, confusion, and hallucinations. Serotonin syndrome, seizures, cerebral vascular accidents, and coma may occur.
- Life-threatening hyperthermia (temperatures greater than 104°F) and rhabdomyolysis may develop.

10.2 Overdose Management

Consider the possibility of multiple drug ingestion. The pharmacokinetic profile of CONCERTA should be considered when treating patients with overdose. Because methylphenidate has a large volume of distribution and is rapidly metabolized, dialysis is not useful. Consider contacting the Poison Help line (1-800-222-1222) or a medical toxicologist for additional overdose management recommendations.

11 DESCRIPTION

CONCERTA® is a central nervous system (CNS) stimulant. CONCERTA is available in four strengths. Each extended-release tablet for oral administration contains 18, 27, 36, or 54 mg of methylphenidate hydrochloride, USP. Chemically, methylphenidate hydrochloride is d,l (racemic) methyl α-phenyl-2-piperidineacetate hydrochloride, its empirical formula is C14H19NO2∙HCl, and its structural formula is:

Methylphenidate hydrochloride, USP is a white, odorless crystalline powder. Its solutions are acid to litmus. It is freely soluble in water and in methanol, soluble in alcohol, and slightly soluble in chloroform and in acetone. Its molecular weight is 269.77.

CONCERTA also contains the following inactive ingredients: butylated hydroxytoluene, carnauba wax, cellulose acetate, hypromellose, lactose, phosphoric acid, poloxamer, polyethylene glycol, polyethylene oxides, povidone, propylene glycol, sodium chloride, stearic acid, succinic acid, synthetic iron oxides, titanium dioxide, and triacetin.

It is possible that CONCERTA extended-release tablets may be visible on abdominal x-rays under certain circumstances, especially when digital enhancing techniques are utilized.

12 CLINICAL PHARMACOLOGY

12.1 Mechanism of Action

Methylphenidate is a central nervous system (CNS) stimulant. The mode of therapeutic action of methylphenidate in the treatment of ADHD is not known. Methylphenidate blocks the reuptake of norepinephrine and dopamine into the presynaptic neuron and increases the release of these monoamines into the extraneuronal space.

12.2 Pharmacodynamics

Methylphenidate is a racemic mixture comprised of the d- and l-isomers. The d-isomer is more pharmacologically active than the l-isomer. The exposure-response relationship and time course of pharmacodynamic response for the safety and effectiveness of CONCERTA have not been fully characterized.

12.3 Pharmacokinetics

Absorption

Following oral administration of CONCERTA, plasma methylphenidate concentrations reached an initial maximum concentration at about 1 hour, followed by gradual ascending concentrations over the next 5 to 9 hours, after which a gradual decrease begins. Mean times to reach peak plasma concentrations across all doses of CONCERTA occurred between 6 and 10 hours.

CONCERTA once daily minimizes the fluctuations between peak and trough concentrations associated with immediate-release methylphenidate three times daily [see Figure 1]. No clinically significant difference in methylphenidate exposures was observed following the administration of either CONCERTA once daily and immediate-release methylphenidate three times daily in adults.

Figure 1. Mean Methylphenidate Plasma Concentrations Following a Single 18 mg CONCERTA dose and Immediate-release Methylphenidate 5 mg Doses (Three Doses Administered Every 4 Hours)

The mean single-dose pharmacokinetic parameters in 36 healthy adults following the administration of one 18 mg CONCERTA dose and three 5 mg methylphenidate doses every four hours are summarized in Table 7.

Table 7: Methylphenidate Pharmacokinetic Parameters (Mean ± SD) After CONCERTA and Immediate-release Methylphenidate Dosing in Healthy Adults
Parameters | CONCERTA (18 mg single dose) (n=36) | Immediate-release Methylphenidate (Three 5 mg doses every four hours) (n=35)
Cmax (ng/mL) | 3.7 ± 1.0 | 4.2 ± 1.0
Tmax (h) | 6.8 ± 1.8 | 6.5 ± 1.8
AUCinf (ng∙h/mL) | 41.8 ± 13.9 | 38.0 ± 11.0
t½ (h) | 3.5 ± 0.4 | 3.0 ± 0.5

The methylphenidate pharmacokinetics were evaluated in healthy adults following single- and multiple-doses (steady state) of CONCERTA (up to 144 mg/day (up to 2 times the maximum recommended dose)). The mean half-life was about 3.6 hours. No differences in the pharmacokinetics of CONCERTA were noted following single and repeated once-daily CONCERTA dosing, indicating no significant drug accumulation. The AUC and t1/2 following repeated once-daily dosing are similar to those following a single 18 to 144 mg dose of CONCERTA.

Dose Proportionality

Following administration of CONCERTA in single doses of 18, 36, and 54 mg/day to healthy adults, Cmax and AUC(0–inf) of d-methylphenidate were dose proportional, whereas l-methylphenidate Cmax and AUC(0–inf) increased disproportionately with respect to dose. Following administration of CONCERTA, plasma concentrations of the l-isomer were approximately 1/40 the plasma concentrations of the d-isomer.

In healthy adults, single and multiple doses (once-daily) CONCERTA doses from 54 to 144 mg/day resulted in linear and dose-proportional increases in Cmax and AUCinf for total methylphenidate (MPH) and its major metabolite, α-phenyl-piperidine acetic acid (PPAA). There was no time dependency in the pharmacokinetics of methylphenidate. The ratio of metabolite (PPAA) to parent drug (MPH) was constant across doses from 54 to 144 mg/day, both after single dose and upon multiple dosing.

In a multiple-dose study, after patients aged 13 to 16 with ADHD were administered their prescribed CONCERTA dose (18 to 72 mg/day), mean Cmax and AUCTAU of d- and total methylphenidate increased proportionally with respect to dose.

Food Effects: In patients, there were no differences in either the pharmacokinetics or the pharmacodynamic performance of CONCERTA when administered after a high-fat breakfast.

Distribution

Plasma methylphenidate concentrations in adults and adolescents decline biexponentially following oral CONCERTA administration. The half-life of methylphenidate in adults and adolescents following oral CONCERTA administration was approximately 3.5 hours.

Elimination

Metabolism: In humans, methylphenidate is metabolized primarily by de-esterification to PPAA, which has little or no pharmacologic activity. In adults the metabolism of CONCERTA once daily as evaluated by metabolism to PPAA was similar to that of immediate-release methylphenidate three times daily. The metabolism of single and repeated once-daily doses of CONCERTA was similar.

Excretion: After oral dosing of radiolabeled methylphenidate in humans, about 90% of the radioactivity was recovered in urine. The main urinary metabolite was PPAA, accounting for approximately 80% of the dose.

Alcohol Effect on Methylphenidate Release in CONCERTA

An in vitro study was conducted to explore the effect of alcohol on the release characteristics of methylphenidate from the CONCERTA 18 mg extended-release tablets. At an alcohol concentration up to 40% there was no increased release of methylphenidate in the first hour. The results with the 18 mg extended-release tablet strength are considered representative of the other available tablet strengths.

Specific Populations

Male and Female Patients:

In healthy adults, the mean dose-adjusted AUC(0–inf) values for CONCERTA were 36.7 ng∙h/mL in males and 37.1 ng∙h/mL in females, with no differences noted between the two groups.

Ethnic Groups:

In adults receiving CONCERTA, dose-adjusted AUC(0–inf) was consistent across ethnic groups; however, the sample size was insufficient to detect ethnic variations in pharmacokinetics.

Pediatric Patients:

Increase in pediatric age was associated with increased apparent oral clearance (CL/F) (58% increase in adolescents compared to younger pediatric patients). Some of these differences could be explained by body-weight differences among these populations. This suggests that subjects with higher body weight may have a lower exposure of total methylphenidate at similar doses.

Patients with Renal Impairment

There is no pharmacokinetic information on the use of CONCERTA in patients with renal impairment.

Patients with Hepatic Impairment

There is no pharmacokinetic information on the use of CONCERTA in patients with hepatic impairment.

13 NONCLINICAL TOXICOLOGY

13.1 Carcinogenesis, Mutagenesis, and Impairment of Fertility

Carcinogenesis

In a lifetime carcinogenicity study carried out in B6C3F1 mice, methylphenidate caused an increase in hepatocellular adenomas and, in males only, an increase in hepatoblastomas at a daily dose of approximately 60 mg/kg/day. This dose is approximately 4 times the maximum recommended human dose (MRHD) of CONCERTA given to adults on a mg/m^2 basis. Hepatoblastoma is a relatively rare rodent malignant tumor type. There was no increase in total malignant hepatic tumors. The mouse strain used is sensitive to the development of hepatic tumors, and the significance of these results to humans is unknown.

Methylphenidate did not cause any increases in tumors in a lifetime carcinogenicity study carried out in F344 rats; the highest dose used was approximately 45 mg/kg/day, which is approximately 6 times the MRHD (adults) on a mg/m^2 basis.

In a 24-week carcinogenicity study in the transgenic mouse strain p53+/-, which is sensitive to genotoxic carcinogens, there was no evidence of carcinogenicity. Male and female mice were fed diets containing the same concentration of methylphenidate as in the lifetime carcinogenicity study; the high-dose groups were exposed to 60 to 74 mg/kg/day of methylphenidate.

Mutagenesis

Methylphenidate was not mutagenic in the in vitro Ames reverse mutation assay or the in vitro mouse lymphoma cell forward mutation assay. Sister chromatid exchanges and chromosome aberrations were increased, indicative of a weak clastogenic response, in an in vitro assay in cultured Chinese Hamster Ovary cells. Methylphenidate was negative in vivo in males and females in the mouse bone marrow micronucleus assay.

Impairment of Fertility

Methylphenidate did not impair fertility in male or female mice that were fed diets containing the drug in an 18-week continuous breeding study. The study was conducted at doses up to 160 mg/kg/day, approximately 11 times the MRHD of CONCERTA given to adults on a mg/m^2 basis.

14 CLINICAL STUDIES

14.1 Overview of Clinical Trials

CONCERTA was demonstrated to be effective in the treatment of ADHD in patients who met the Diagnostic and Statistical Manual 4th edition (DSM-IV) criteria for ADHD in the following trials:

- Three trials in pediatric patients 6 to 12 years old (Studies 1, 2, and 3),
- One trial in adolescents (13 to 18 years old),
- Two trials in adults (18 to 65 years old).

14.2 Clinical Trials in Pediatric Patients 6 to 12 Years

Three double-blind, active- and placebo-controlled trials were conducted in 416 pediatric patients 6 to 12 years of age with ADHD: (1) two single-center, crossover trials (patients received each treatment for one week) (Studies 1 and 2) and (2) a multicenter, 4-week, parallel-group comparison trial (Study 3). In these trials, patients were randomized to receive:

- 18 mg, 36 mg, or 54 mg of oral CONCERTA given once daily,
- 5 mg, 10 mg, or 15 mg of oral immediate-release methylphenidate given three times daily (15, 30, or 45 mg total daily dosage) over 12 hours, and
- Placebo

The primary comparison of interest in all three trials was the CONCERTA group versus the placebo group.

ADHD symptoms were evaluated by community schoolteachers using the Inattention/Overactivity with Aggression (IOWA) Conners scale.

A statistically significant reduction in the Inattention/Overactivity subscale (0 to 15) in the CONCERTA group versus the placebo group was shown in all three trials. The scores for CONCERTA and placebo for the three trials are presented in Figure 2.

Figure 2. Mean Community School Teacher Inattention/Overactivity Subscores in the IOWA Conners Scale in Pediatric Patients 6 to 12 Years with ADHD

Studies 1 and 2 involved a 3-way crossover of 1-week per treatment arm. Study 3 involved 4 weeks of parallel-group treatments with a Last Observation Carried Forward analysis at week 4. Error bars represent the mean plus standard error of the mean.

In Studies 1 and 2, symptoms of ADHD including attentiveness were evaluated by schoolteachers using the Swanson, Kotkin, Agler, M-Fynn, and Pelham (SKAMP) laboratory school rating scale. The combined results from these two trials demonstrated statistically significant improvements in attention and behavior in the CONCERTA group compared to the placebo group. These results were maintained through 12 hours after dosing. Figure 3 presents the schoolteacher SKAMP ratings for the CONCERTA and placebo groups in Studies 1 and 2.

Figure 3. School Teacher SKAMP Ratings (Mean (SEM) of Combined Attention) in Pediatric Patients 6 to 12 Years with ADHD (Studies 1 and 2)

14.3 Clinical Trials in Pediatric Patients 13 to 17 Years

In a randomized-withdrawal, double-blind, multicenter, placebo-controlled trial (Study 4) with 177 pediatric patients 13 to 17 years of age with ADHD, CONCERTA demonstrated effectiveness with a dosage up to 72 mg/day (1.4 mg/kg/day):

- Of 220 patients who entered an open 4-week titration phase, 177 patients were titrated to an individualized CONCERTA dosage (maximum of 72 mg/day) based on meeting specific improvement criteria on the ADHD Rating Scale and the Global Assessment of Effectiveness with acceptable tolerability.
- Patients who met these criteria were then randomized to receive either their individualized dosage of CONCERTA (18 – 72 mg/day, n=87) or placebo (n=90) during a two-week double-blind phase.

At the end of the double blind phase, mean scores for the investigator rating on the ADHD Rating Scale demonstrated that the CONCERTA group was statistically significantly superior to the placebo group.

14.4 Clinical Trials in Adults up to 65 Years Old

Two randomized double-blind, placebo-controlled multicenter, parallel-group trials were conducted in 627 adults aged 18 to 65 years with ADHD who received CONCERTA or placebo once daily:

- Study 5 was a 7-week, dose-titration trial where patients were randomized to receive CONCERTA (n=110) or placebo (n=116) once daily. Patients treated with CONCERTA started at 36 mg/day and had incremental increases of 18 mg/day up to 108 mg/day of CONCERTA (titration was based on improvement criteria with acceptable tolerability).
- Study 6 was a 5-week, fixed-dose trial where patients were randomized to receive 18 mg (n=101), 36 mg (n=102), or 72 mg (n=102) of CONCERTA versus placebo (n=96) once daily.

In Study 5, CONCERTA demonstrated efficacy based on the change from baseline to final study visit on the Adult ADHD Investigator Rating Scale (AISRS). At the final study visit, mean change scores (LS Mean, SEM) for the investigator rating on the AISRS demonstrated that the CONCERTA group was statistically significantly superior to the placebo group.

In Study 6, all three CONCERTA dosages were statistically significantly more effective than placebo in improving Conners' Adult ADHD Rating Scale (CAARS) total scores after five weeks of treatment.

16 HOW SUPPLIED/STORAGE AND HANDLING

CONCERTA® (methylphenidate hydrochloride) extended-release tablets are available in 18 mg, 27 mg, 36 mg, and 54 mg strengths:

- 18 mg: yellow and imprinted with "alza 18", 100-count bottle (NDC 50458-585-01)
- 27 mg: gray and imprinted with "alza 27", 100-count bottle (NDC 50458-588-01)
- 36 mg: white and imprinted with "alza 36", 100-count bottle (NDC 50458-586-01)
- 54 mg: brownish-red and imprinted with "alza 54", 100-count bottle (NDC 50458-587-01)

Storage and Handling

Store at 25 °C (77 °F); excursions permitted to 15–30 °C (59–86 °F) [see USP Controlled Room Temperature]. Protect from humidity.

17 PATIENT COUNSELING INFORMATION

Advise the patient to read the FDA-approved patient labeling (Medication Guide).

Abuse, Misuse, and Addiction

Educate patients and their families about the risks of abuse, misuse, and addiction of CONCERTA, which can lead to overdose and death, and proper disposal of any unused drug [see Warnings and Precautions (5.1), Drug Abuse and Dependence (9.1, 9.2), Overdosage (10)]. Advise patients to store CONCERTA in a safe place, preferably locked, and instruct patients to not give CONCERTA to anyone else.

Risks to Patients with Serious Cardiac Disease

Advise patients that there are potential risks to patients with serious cardiac disease, including sudden death, with CONCERTA use. Instruct patients to contact a healthcare provider immediately if they develop symptoms such as exertional chest pain, unexplained syncope, or other symptoms suggestive of cardiac disease [see Warnings and Precautions (5.2)].

Increased Blood Pressure and Heart Rate

Advise patients and their caregivers that CONCERTA can cause elevations in blood pressure and heart rate [see Warnings and Precautions (5.3)].

Psychiatric Risks

Advise patients and their caregivers that CONCERTA, at recommended doses, can cause psychotic or manic symptoms, even in patients without a prior history of psychotic symptoms or mania [see Warnings and Precautions (5.4)].

Priapism

Advise patients, caregivers, and family members of CONCERTA-treated males of the possibility of priapism. Instruct the patient to seek immediate medical attention in the event of priapism [see Warnings and Precautions (5.5)].

Peripheral Vasculopathy, including Raynaud's Phenomenon

Instruct patients about the risk of peripheral vasculopathy, including Raynaud's phenomenon, and associated signs and symptoms; to report to their health care provider any new numbness, pain, skin color change, or sensitivity to temperature in fingers or toes; to call their health care provider immediately with any signs of unexplained wounds appearing on fingers or toes while taking CONCERTA [see Warnings and Precautions (5.6)].

Long-term Suppression of Growth in Pediatric Patients

Advise patients, caregivers, and family members that CONCERTA may cause slowing of growth and weight loss in pediatric patients [see Warnings and Precautions (5.7)].

Glaucoma and Increased Intraocular Pressure

Advise patients that increased intraocular pressure and glaucoma may occur during CONCERTA treatment [see Warnings and Precautions (5.10)].

Motor and Verbal Tics, and Worsening of Tourette's Syndrome

Advise patients that motor and verbal tics and worsening of Tourette's Syndrome may occur during CONCERTA treatment. Instruct patients to notify their healthcare provider if emergence of new tics or worsening of tics or Tourette's syndrome occurs [see Warnings and Precautions (5.11)].

Administration Instructions

Instruct patients to swallow CONCERTA whole with liquids, and not to split, crush, or chew, the extended-release tablets. Advise patients not to be concerned if they occasionally notice a tablet-appearing substance in their stool.

Pregnancy

Advise patients that there is a pregnancy exposure registry that monitors pregnancy outcomes in women exposed to CONCERTA during pregnancy [see Use in Specific Populations (8.1)].

Lactation

Advise CONCERTA-treated breastfeeding women to monitor their infants for agitation, poor sleeping patterns, changes in feeding, and reduced weight gain [see Use in Specific Populations (8.2)].

Manufactured for:
Janssen Pharmaceuticals, Inc.
Titusville, NJ 08560, USA

For patent information: www.janssenpatents.com
© Johnson and Johnson and its affiliates 2026

For more information about CONCERTA call 1-800-526-7736.

MEDICATION GUIDE
CONCERTA® (kon SER-ta)
(methylphenidate hydrochloride) extended-release tablets
for oral use, CII

What is the most important information I should know about CONCERTA?
CONCERTA may cause serious side effects, including:

- Abuse, misuse, and addiction. CONCERTA has a high chance for abuse and misuse and may lead to substance use problems, including addiction. Misuse and abuse of CONCERTA, other methylphenidate containing medicines, and amphetamine containing medicines, can lead to overdose and death. The risk of overdose and death is increased with higher doses of CONCERTA or when it is used in ways that are not approved, such as snorting or injection.
  - Your healthcare provider should check you or your child's risk for abuse, misuse, and addiction before starting treatment with CONCERTA and will monitor you or your child during treatment.
  - CONCERTA may lead to physical dependence after prolonged use, even if taken as directed by your healthcare provider.
  - Do not give CONCERTA to anyone else. See "What is CONCERTA?" for more information.
  - Keep CONCERTA in a safe place and properly dispose of any unused medicine. See "How should I store CONCERTA?" for more information.
  - Tell your healthcare provider if you or your child have ever abused or been dependent on alcohol, prescription medicines, or street drugs.
- Risks for people with serious heart disease. Sudden death has happened in people who have heart defects or other serious heart disease.
  Your healthcare provider should check you or your child carefully for heart problems before starting treatment with CONCERTA. Tell your healthcare provider if you or your child have any heart problems, heart disease, or heart defects.
  Call your healthcare provider or go to the nearest hospital emergency room right away if you or your child have any signs of heart problems, such as chest pain, shortness of breath, or fainting during treatment with CONCERTA.
- Increased blood pressure and heart rate.
  Your healthcare provider should check your or your child's blood pressure and heart rate regularly during treatment with CONCERTA.
- Mental (psychiatric) problems, including:
  - new or worse behavior or thought problems
  - new or worse bipolar illness
  - new psychotic symptoms (such as hearing voices, or seeing or believing things that are not real) or new manic symptoms
  Tell your healthcare provider about any mental problems you or your child have, or about a family history of suicide, bipolar illness, or depression.
  Call your healthcare provider right away if you or your child have any new or worsening mental symptoms or problems during treatment with CONCERTA, especially hearing voices, seeing or believing things that are not real, or new manic symptoms.

See "What are the possible side effects of CONCERTA?" for more information about side effects.

What is CONCERTA?
CONCERTA is a central nervous system (CNS) stimulant prescription medicine used for the treatment of attention deficit hyperactivity disorder (ADHD) in people 6 to 65 years of age. CONCERTA may help increase attention and decrease impulsiveness and hyperactivity in people with ADHD.
CONCERTA is not recommended for use in children under 6 years of age with ADHD.
CONCERTA is a federally controlled substance (CII) because it contains methylphenidate that can be a target for people who abuse prescription medicines or street drugs. Keep CONCERTA in a safe place to protect it from theft. Never give your CONCERTA to anyone else because it may cause death or harm them. Selling or giving away CONCERTA may harm others and is against the law.

Who should not take CONCERTA?
Do not take CONCERTA if you or your child are:

- allergic to methylphenidate or any of the ingredients in CONCERTA. See the end of this Medication Guide for a complete list of ingredients in CONCERTA.
- taking, or have stopped taking within the past 14 days, a medicine called a monoamine oxidase inhibitor (MAOI)

Before taking CONCERTA, tell your healthcare provider about all of your or your child's medical conditions, including if you or your child:

- have heart problems, heart disease, heart defects, or high blood pressure
- have mental problems including psychosis, mania, bipolar illness, or depression, or have a family history of suicide, bipolar illness, or depression
- have circulation problems in fingers and toes
- have had a blockage or narrowing of the intestines
- have eye problems, including increased pressure in your eye, glaucoma, or problems with your close-up vision (farsightedness)
- have or had repeated movements or sounds (tics) or Tourette's syndrome, or have a family history of tics or Tourette's syndrome
- are pregnant or plan to become pregnant. It is not known if CONCERTA will harm the unborn baby.
  - There is a pregnancy exposure registry for women are exposed to CONCERTA during pregnancy. The purpose of the registry is to collect information about the health of women exposed to CONCERTA and their baby. If you or your child becomes pregnant during treatment with CONCERTA, talk to your healthcare provider about registering with the National Pregnancy Registry for ADHD Medications at 1-866-961-2388 or visit online at https://womensmentalhealth.org/adhd-medications/.
- are breastfeeding or plan to breastfeed. CONCERTA passes into the breast milk. Talk to your healthcare provider about the best way to feed the baby during treatment with CONCERTA. If you breastfeed during treatment with CONCERTA, monitor your baby for agitation, poor sleeping patterns, changes in feeding, and reduced weight gain.

Tell your healthcare provider about all of the medicines that you or your child take, including prescription and over-the-counter medicines, vitamins, and herbal supplements.
CONCERTA and some medicines may interact with each other and cause serious side effects. Sometimes the doses of other medicines will need to be changed during treatment with CONCERTA. Your healthcare provider will decide whether CONCERTA can be taken with other medicines.
Especially tell your healthcare provider if you or your child take:

- a medicine to treat blood pressure (anti-hypertensive)
- risperidone

Know the medicines that you or your child take. Keep a list of your or your child's medicines with you to show your healthcare provider and pharmacist when you or your child get a new medicine.
Do not start any new medicine during treatment with CONCERTA without first talking to your healthcare provider.

How should I take CONCERTA?

- Take CONCERTA exactly as prescribed by your or your child's healthcare provider.
- Your healthcare provider may change the dose or tell you to stop taking CONCERTA if needed.
- Take CONCERTA 1 time each day in the morning with or without food.
- Swallow CONCERTA tablets whole with water or other liquids. Do not split, crush, or chew the tablets. Tell your healthcare provider if you or your child cannot swallow CONCERTA tablets whole. A different medicine will need to be prescribed.
- CONCERTA does not dissolve completely in the body after all the medicine has been released. You or your child may sometimes notice the empty tablet in a bowel movement. This is normal.
- If you or your child take too much CONCERTA, call your healthcare provider or Poison Help line at 1-800-222-1222 or go to the nearest hospital emergency room right away.

What are the possible side effects of CONCERTA?
CONCERTA may cause serious side effects, including:

- See "What is the most important information I should know about CONCERTA?"
- Painful and prolonged erections (priapism). Priapism that may require surgery has happened in males who take products that contain methylphenidate. If you or your child develop priapism, get medical help right away.
- Circulation problems in fingers and toes (peripheral vasculopathy, including Raynaud's phenomenon). Signs and symptoms may include:
  - fingers or toes may feel numb, cool, painful
  - fingers or toes may change color from pale, to blue, to red
  Tell your healthcare provider if you or your child have any numbness, pain, skin color change, or sensitivity to temperature in your fingers or toes.
  Call your healthcare provider right away if you or your child have any signs of unexplained wounds appearing on fingers or toes during treatment with CONCERTA.
- Slowing of growth (height and weight) in children. Children should have their height and weight checked often during treatment with CONCERTA. CONCERTA treatment may be stopped if your child is not growing or gaining weight as expected.
- Risk of intestinal blockage in people with narrowed digestive tract (gastrointestinal narrowing). Because the CONCERTA tablet does not change in shape in the intestines (GI tract), CONCERTA should not be taken by people with severe intestinal problems (pre-existing severe gastrointestinal narrowing).
- Eye problems (increased pressure in the eye and glaucoma). Call your healthcare provider right away if you or your child develop changes in your vision or eye pain, swelling, or redness.
- New or worsening tics or worsening Tourette's syndrome. Tell your healthcare provider if you or your child get any new or worsening tics or worsening Tourette's syndrome during treatment with CONCERTA.

The most common side effect of CONCERTA in children 6 to 17 years of age is upper stomach-area (abdominal) pain.
The most common side effects of CONCERTA in adults up to 65 years of age include:

- decreased appetite
- headache
- dry mouth
- nausea
- trouble sleeping
- anxiety

- dizziness
- weight loss
- irritability
- fast heart beat
- increased sweating

These are not all the possible side effects of CONCERTA.
Call your doctor for medical advice about side effects. You may report side effects to FDA at 1-800-FDA-1088.
You may also report side effects to Janssen Pharmaceuticals, Inc. at 1-800-JANSSEN (1-800-526-7736).

How should I store CONCERTA?

- Store CONCERTA at room temperature between 59 °F to 86 °F (15 °C to 30 °C).
- Protect from moisture.
- Store CONCERTA in a safe place, like a locked cabinet.
- Dispose of remaining, unused, or expired CONCERTA by a medicine take-back program at a U.S. Drug Enforcement Administration (DEA) authorized collection site. If no take-back program or DEA authorized collector is available, mix CONCERTA with an undesirable, nontoxic substance such as dirt, cat litter, or used coffee grounds to make it less appealing to children and pets. Place the mixture in a container such as a sealed plastic bag and throw away CONCERTA in the household trash. Visit www.fda.gov/drugdisposal for additional information on disposal of unused medicines.

Keep CONCERTA and all medicines out of the reach of children.

General information about the safe and effective use of CONCERTA.
Medicines are sometimes prescribed for purposes other than those listed in a Medication Guide. Do not use CONCERTA for a condition for which it was not prescribed. Do not give CONCERTA to other people, even if they have the same condition. It may harm them and it is against the law.
You can ask your pharmacist or healthcare provider for information about CONCERTA that is written for health professionals.

What are the ingredients in CONCERTA?
Active ingredient: methylphenidate hydrochloride
Inactive ingredients: butylated hydroxytoluene, carnauba wax, cellulose acetate, hypromellose, lactose, phosphoric acid, poloxamer, polyethylene glycol, polyethylene oxides, povidone, propylene glycol, sodium chloride, stearic acid, succinic acid, synthetic iron oxides, titanium dioxide, and triacetin.
Manufactured for: Janssen Pharmaceuticals, Inc., Titusville, NJ 08560, USA
For patent information: www.janssenpatents.com
© Johnson and Johnson and its affiliates 2026
For more information, go to www.concerta.net or call 1-800-JANSSEN (1-800-526-7736).

This Medication Guide has been approved by the U.S. Food and Drug Administration.

Revised: 02/2026

PRINCIPAL DISPLAY PANEL - 18 mg Tablet Bottle Label

NDC 50458-585-01

CONCERTA®
(methylphenidate HCl)
CII

Extended-release tablets

18 mg

Each tablet contains 18 mg
methylphenidate hydrochloride
in a controlled-release formulation.

Please see the Medication Guide
provided by your pharmacist.

Rx only
100 Tablets

janssen

PRINCIPAL DISPLAY PANEL - 27 mg Tablet Bottle Label

NDC 50458-588-01

CONCERTA®
(methylphenidate HCl)
CII

Extended-release tablets

27 mg

Each tablet contains 27 mg
methylphenidate hydrochloride
in a controlled-release formulation.

Please see the Medication Guide
provided by your pharmacist.

Rx only
100 Tablets

janssen

PRINCIPAL DISPLAY PANEL - 36 mg Tablet Bottle Label

NDC 50458-586-01

CONCERTA ®
(methylphenidate HCl)
CII

Extended-release tablets

36 mg

Each tablet contains 36 mg
methylphenidate hydrochloride
in a controlled-release formulation.

Please see the Medication Guide
provided by your pharmacist.

Rx only
100 Tablets

janssen

PRINCIPAL DISPLAY PANEL - 54 mg Tablet Bottle Label

NDC 50458-587-01

CONCERTA®
(methylphenidate HCl)
CII

Extended-release tablets

54 mg

Each tablet contains 54 mg
methylphenidate hydrochloride
in a controlled-release formulation.

Please see the Medication Guide
provided by your pharmacist.

Rx only
100 Tablets

janssen